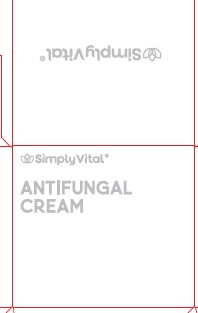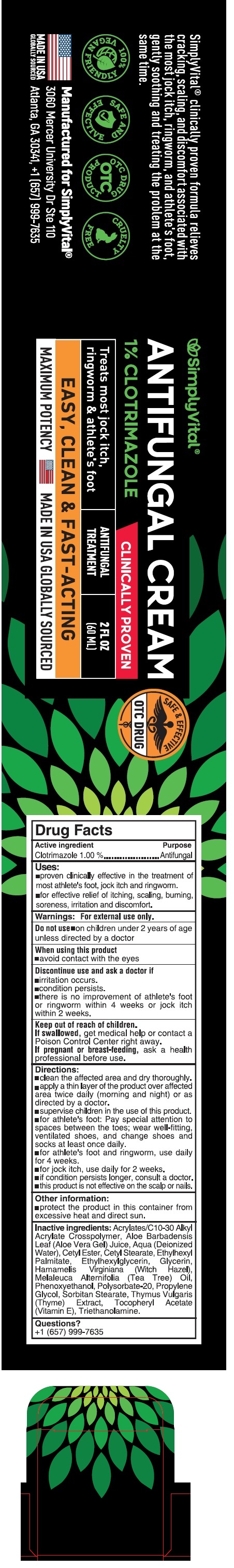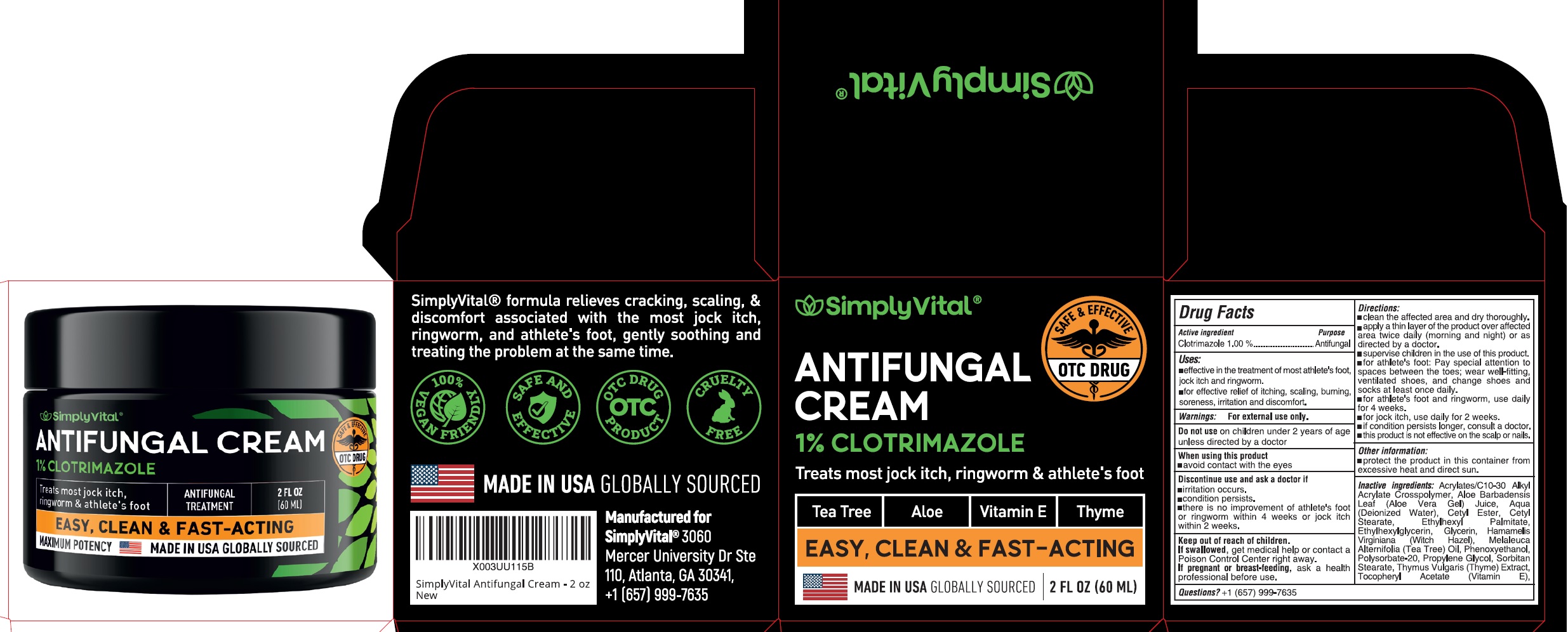 DRUG LABEL: Simply Vital Antifungal Clotrimazole
NDC: 82460-990 | Form: CREAM
Manufacturer: Alpha Plants Inc
Category: otc | Type: HUMAN OTC DRUG LABEL
Date: 20260128

ACTIVE INGREDIENTS: CLOTRIMAZOLE 10 mg/1 mL
INACTIVE INGREDIENTS: ALOE VERA LEAF JUICE; WATER; CETYL STEARATE; ETHYLHEXYL PALMITATE; ETHYLHEXYLGLYCERIN; GLYCERIN; HAMAMELIS VIRGINIANA ROOT BARK/STEM BARK; TEA TREE OIL; PHENOXYETHANOL; POLYSORBATE 20; PROPYLENE GLYCOL; SORBITAN MONOSTEARATE; THYME; .ALPHA.-TOCOPHEROL ACETATE; TROLAMINE

Simply Vital Antifungal Cream 1% Clotrimazole

Active ingredient

Clotrimazole 1.00%

Purpose

Antifungal

Uses:

- effective in the treatment of most athlete's foot, jock itch and ringworm.
- for effective relief of itching, scaling, burning, soreness, irritation and doscomfort.

Warnings:

For external use only.

Do not use

- on children under 2 years of age unless directed by a doctor

When using this product

- Avoid contact with the eyes

Discontinue use and ask a doctor if

- irritation occurs.
- condition persists.
- there is no improvement of athelete's foot or ringworm within 4 weeks or jock itch within 2 weeks.

Keep out of reach of children.

If swallowed, get medical help or contact a Poison Control Center right away.

If pregnant or breast-feeding,

ask a health professional before use.

Directions:

- clean the affected area and dry thoroughly.
- apply a thin layer of the product over affected area twice daily (morning and night) or as directed by a doctor.
- supervise children in the use of this product.
- for athelete's foot: pay special attention to spaces between the toes; wear well-fitting, ventilated shoes, and change shoes and socks at least once daily.
- for athelete's foot and ringworm, use daily for 4 weeks.
- for jock itch, use daily for 2 weeks.
- if condition persists longer, consult a doctor.
- this product is not effective on the scalp or nails.

Other information:

- protect the product in this container from excessive heat and direct sun.

Inactive ingredients:

Acrylates/C 10-30 Alkyl Acrylate Crosspolymer, Aloe Barbadensis Leaf (Aloe Vera Gel) Juice, Aqua (Deionized Water), Cetyl Ester, Cetyl Stearate, Ethylhexyl Palmitate, Ethylhexylglycerin, Glycerin, Hamamelis Virginiana (Witch Hazel), Melaleuca Alternifolia (Tea Tree) Oil, Phenoxyethanol, Polysorbate-20, Propylene Glycol, Sorbitan Stearate, Thymus Vulgaris (Thyme) Extract, Tocopheryl Acetate (Vitamin E), Triethanolamine.

Questions?

+1 (657) 999-7635